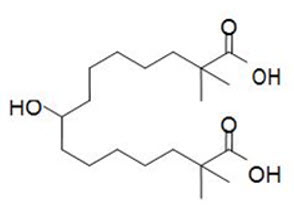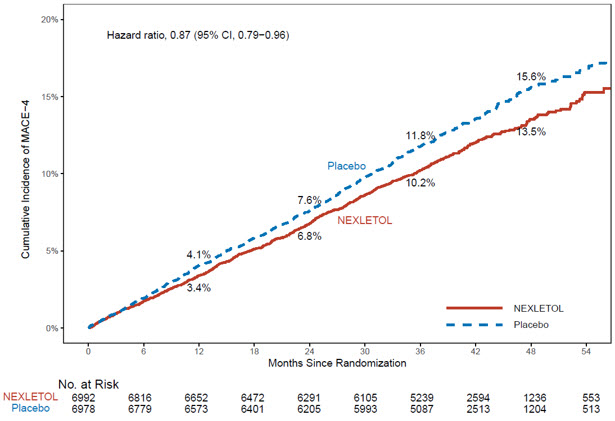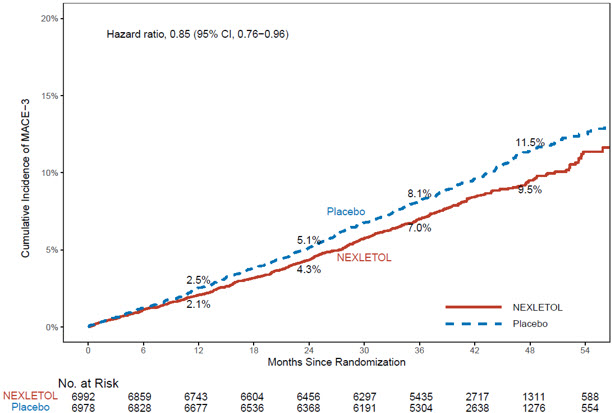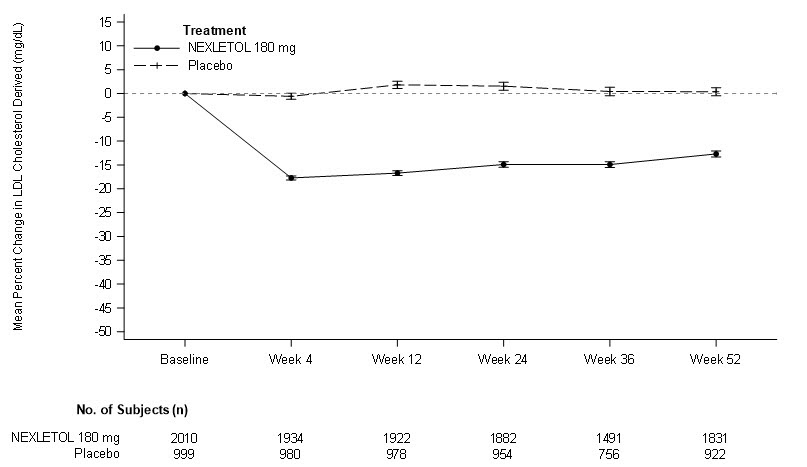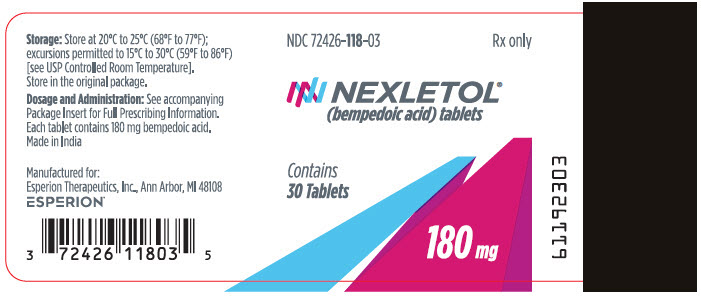 DRUG LABEL: Nexletol
NDC: 72426-118 | Form: TABLET, FILM COATED
Manufacturer: Esperion Therapeutics, Inc.
Category: prescription | Type: HUMAN PRESCRIPTION DRUG LABEL
Date: 20260115

ACTIVE INGREDIENTS: BEMPEDOIC ACID 180 mg/1 1
INACTIVE INGREDIENTS: MICROCRYSTALLINE CELLULOSE 101; LACTOSE MONOHYDRATE; HYDROXYPROPYL CELLULOSE, UNSPECIFIED; SILICON DIOXIDE; SODIUM STARCH GLYCOLATE TYPE A POTATO; MAGNESIUM STEARATE; POLYVINYL ALCOHOL, UNSPECIFIED; TITANIUM DIOXIDE; POLYETHYLENE GLYCOL, UNSPECIFIED; TALC

HIGHLIGHTS OF PRESCRIBING INFORMATION

These highlights do not include all the information needed to use NEXLETOL® safely and effectively. See full prescribing information for NEXLETOL.
NEXLETOL (bempedoic acid) tablets, for oral use
Initial U.S. Approval: 2020

RECENT MAJOR CHANGES

Indications and Usage (1) | 11/2025

1 INDICATIONS AND USAGE

NEXLETOL, an adenosine triphosphate-citrate lyase (ACL) inhibitor, is indicated:

- to reduce the risk of major adverse cardiovascular events (cardiovascular death, myocardial infarction, stroke, or coronary revascularization) in adults at increased risk for these events who are unable to take recommended statin therapy (including those not taking a statin). (1)
- as an adjunct to diet and exercise, in combination with other low-density lipoprotein cholesterol (LDL-C) lowering therapies, or alone when concomitant LDL-C lowering therapy is not possible, to reduce LDL-C in adults with hypercholesterolemia, including heterozygous familial hypercholesterolemia (HeFH). (1)

2 DOSAGE AND ADMINISTRATION

Administer 180 mg orally once daily with or without food. (2.1)

3 DOSAGE FORMS AND STRENGTHS

Tablets: 180 mg (3)

4 CONTRAINDICATIONS

History of a serious hypersensitivity reaction to bempedoic acid or any of the excipients in NEXLETOL. (4)

5 WARNINGS AND PRECAUTIONS

Hyperuricemia: Elevations in serum uric acid have occurred. Assess uric acid levels periodically as clinically indicated. Monitor for signs and symptoms of hyperuricemia, and initiate treatment with urate-lowering drugs as appropriate. (5.1)

Tendon Rupture: Tendon rupture has occurred. Discontinue NEXLETOL at the first sign of tendon rupture. Avoid NEXLETOL in patients who have a history of tendon disorders or tendon rupture. (5.2)

6 ADVERSE REACTIONS

Common adverse reactions in the (6.1):

- Primary hypercholesterolemia trials (incidence ≥ 2% and more frequent than placebo) were upper respiratory tract infection, muscle spasms, hyperuricemia, back pain, abdominal pain or discomfort, bronchitis, pain in extremity, anemia, and elevated liver enzymes.
- Cardiovascular outcomes trial (incidence ≥ 2% and 0.5% greater than placebo) were hyperuricemia, renal impairment, anemia, elevated liver enzymes, muscle spasms, gout, and cholelithiasis.

To report SUSPECTED ADVERSE REACTIONS, contact Esperion at 833-377-7633 (833 ESPRMED) or FDA at 1-800-FDA-1088 or www.fda.gov/medwatch.

7 DRUG INTERACTIONS

- Simvastatin: Avoid concomitant use of NEXLETOL with simvastatin greater than 20 mg. (7)
- Pravastatin: Avoid concomitant use of NEXLETOL with pravastatin greater than 40 mg. (7)
- Fibrates: Concomitant use of NEXLETOL with fibrates may increase triglycerides and decrease high-density lipoprotein cholesterol. (7)

8 USE IN SPECIFIC POPULATIONS

- Pregnancy: Based on mechanism of action, may cause fetal harm. (8.1)

FULL PRESCRIBING INFORMATION

1 INDICATIONS AND USAGE

NEXLETOL is indicated:

- to reduce the risk of major adverse cardiovascular events (cardiovascular death, myocardial infarction, stroke, or coronary revascularization) in adults at increased risk for these events who are unable to take recommended statin therapy (including those not taking a statin).
- as an adjunct to diet and exercise, in combination with other low-density lipoprotein cholesterol (LDL-C) lowering therapies, or alone when concomitant LDL-C lowering therapy is not possible, to reduce LDL-C in adults with hypercholesterolemia, including heterozygous familial hypercholesterolemia (HeFH).

2 DOSAGE AND ADMINISTRATION

2.1 Recommended Dosage

The recommended dosage of NEXLETOL is 180 mg administered orally once daily. NEXLETOL can be taken with or without food.

After initiation of NEXLETOL, analyze lipid levels within 8 to 12 weeks.

3 DOSAGE FORMS AND STRENGTHS

NEXLETOL is available as:

- Tablets: 180 mg, white to off-white, oval shaped, debossed with "180" on one side and "ESP" on the other side.

4 CONTRAINDICATIONS

NEXLETOL is contraindicated in patients with a prior serious hypersensitivity reaction to bempedoic acid or any of the excipients in NEXLETOL. Serious hypersensitivity reactions, such as angioedema, have occurred [see Adverse Reactions (6.2)].

5 WARNINGS AND PRECAUTIONS

5.1 Hyperuricemia

NEXLETOL inhibits renal tubular OAT2 and may increase blood uric acid levels [see Clinical Pharmacology (12.3)]. In the primary hypercholesterolemia trials [see Clinical Studies (14.2)], 26% of NEXLETOL-treated patients with normal baseline uric acid values (versus 9.5% placebo) experienced hyperuricemia one or more times, and 3.5% of patients experienced clinically significant hyperuricemia reported as an adverse reaction (versus 1.1% placebo). Increases in uric acid levels usually occurred within the first 4 weeks of treatment initiation, persisted throughout treatment, and returned to baseline following discontinuation of treatment. After 12 weeks of treatment, the mean placebo-adjusted increase in uric acid compared to baseline was 0.8 mg/dL for patients treated with NEXLETOL. In the cardiovascular outcomes trial [see Clinical Studies (14.1)], 16.4% of NEXLETOL-treated patients experienced clinically significant hyperuricemia reported as an adverse reaction (versus 8.2% placebo).

Elevated blood uric acid may lead to the development of gout. In the primary hypercholesterolemia trials, gout was reported in 1.5% of patients treated with NEXLETOL and 0.4% of patients treated with placebo. In the cardiovascular outcomes trial, gout was reported in 3.2% of patients treated with NEXLETOL and 2.2% treated with placebo.

Advise patients to contact their healthcare provider if symptoms of hyperuricemia occur. Assess serum uric acid when clinically indicated. Monitor patients for signs and symptoms of hyperuricemia, and initiate treatment with urate-lowering drugs as appropriate.

5.2 Tendon Rupture

NEXLETOL is associated with an increased risk of tendon rupture or injury. In the primary hypercholesterolemia trials [see Clinical Studies (14.2)], tendon rupture occurred in 0.5% of patients treated with NEXLETOL versus 0% of placebo-treated patients and involved the rotator cuff (the shoulder), biceps tendon, or Achilles tendon. Tendon rupture occurred within weeks to months of starting NEXLETOL. In the cardiovascular outcomes trial [see Clinical Studies (14.1)], tendon rupture events occurred in 1.2% of NEXLETOL-treated patients versus 0.9% of placebo-treated patients. Tendon rupture may occur more frequently in patients over 60 years of age, in those taking corticosteroid or fluoroquinolone drugs, in patients with renal failure, and in patients with previous tendon disorders.

Discontinue NEXLETOL immediately if the patient experiences rupture of a tendon. Consider discontinuing NEXLETOL if the patient experiences joint pain, swelling, or inflammation. Advise patients to rest at the first sign of tendinitis or tendon rupture and to contact their healthcare provider if tendinitis or tendon rupture symptoms occur. Consider alternative therapy in patients with a history of tendon disorders or tendon rupture.

6 ADVERSE REACTIONS

The following clinically significant adverse reactions are described elsewhere in the labeling:

- Hyperuricemia [see Warnings and Precautions (5.1)]
- Tendon Rupture [see Warnings and Precautions (5.2)]

6.1 Clinical Trials Experience

Because clinical trials are conducted under widely varying conditions, adverse reaction rates observed in the clinical trials of a drug cannot be directly compared to rates in the clinical trials of another drug and may not reflect the rates observed in clinical practice.

The data in Table 1 reflect exposure to NEXLETOL in two placebo-controlled primary hypercholesterolemia trials that included 2,009 patients treated with NEXLETOL for 52 weeks (median treatment duration of 52 weeks) [see Clinical Studies (14.2)]. The mean age for NEXLETOL-treated patients was 65 years, 29% were female, 95% were White, 3% were Black or African American, 1% were Asian, and 1% were other races; 3% identified as Hispanic or Latino ethnicity. All patients received NEXLETOL 180 mg orally once daily plus maximally tolerated statin therapy alone or in combination with other lipid-lowering therapies. At baseline, 97% of patients had CVD and about 4% had a diagnosis of HeFH. Patients on simvastatin 40 mg/day or higher were excluded from the trials.

In the primary hypercholesterolemia trials, adverse reactions led to discontinuation of treatment in 11% of NEXLETOL-treated patients and 8% of placebo-treated patients. The most common reasons for NEXLETOL treatment discontinuation were muscle spasms (0.5% versus 0.3% placebo), diarrhea (0.4% versus 0.1% placebo), and pain in extremity (0.3% versus 0.0% placebo). Adverse reactions reported in at least 2% of NEXLETOL-treated patients and more frequently than in placebo-treated patients are shown in Table 1.

Table 1. Adverse Reactions (≥ 2% and greater than placebo) in NEXLETOL-Treated Patients with Primary Hypercholesterolemia and CVD or HeFH (Trials 2 and 3)
Adverse Reaction | Placebo [Background therapy included statin and ± other lipid-lowering therapies] (N = 999) % | NEXLETOL (N = 2,009) %
Upper respiratory tract infection | 4.0 | 4.5
Muscle spasms | 2.3 | 3.6
Hyperuricemia [Grouped term that includes other related terms] | 1.1 | 3.5
Back pain | 2.2 | 3.3
Abdominal pain or discomfort | 2.2 | 3.1
Bronchitis | 2.5 | 3.0
Pain in extremity | 1.7 | 3.0
Anemia | 1.9 | 2.8
Elevated liver enzymes | 0.8 | 2.1

In the cardiovascular outcomes trial, in which 7,001 patients were exposed to NEXLETOL and 6,964 patients were exposed to placebo for a median of 3.1 years [see Clinical Studies, (14.1)], adverse reactions led to discontinuation of treatment in 11% of NEXLETOL-treated patients and 10% of placebo-treated patients. Adverse reactions reported in at least 2% of NEXLETOL-treated patients and 0.5% greater than placebo are shown in Table 2.

Table 2. Adverse Reactions (≥ 2% and 0.5% greater than placebo) in NEXLETOL-Treated Patients with CVD or at High Risk for CVD (Trial 1)
Adverse Reaction | Placebo (N=6,964) % | NEXLETOL (N=7,001) %
Hyperuricemia [Grouped term that includes other related terms] | 8 | 16
Renal impairment [Renal impairment includes laboratory related terms including glomerular filtration rate decreased, blood creatinine increased and hematuria] | 9 | 11
Anemia | 4 | 5
Elevated liver enzymes | 3 | 4
Muscle spasms | 3 | 4
Gout | 2 | 3
Cholelithiasis | 1 | 2

Other Adverse Reactions

Tendon Rupture

In the hypercholesterolemia trials, tendon rupture occurred in 0.5% of NEXLETOL-treated patients versus 0% of placebo-treated patients. In the cardiovascular outcomes trial, tendon rupture events occurred in 1.2% of NEXLETOL-treated patients versus 0.9% of placebo-treated patients.

Gout

In the hypercholesterolemia trials, gout occurred in 1.5% of NEXLETOL-treated patients versus 0.4% of placebo-treated patients. In the cardiovascular outcomes trial, gout occurred in 3.2% of NEXLETOL-treated patients versus 2.2% of placebo-treated patients.

Laboratory Tests

NEXLETOL was associated with persistent changes in multiple laboratory tests that occurred within the first 4 weeks of treatment and returned to baseline following discontinuation of treatment.

Increase in Creatinine and Blood Urea Nitrogen

In the hypercholesterolemia trials, there was a mean increase in serum creatinine of 0.05 mg/dL compared to baseline with NEXLETOL at Week 12. Approximately 3.8% of patients treated with NEXLETOL had blood urea nitrogen values that doubled (versus 1.5% placebo), and about 2.2% of patients had creatinine values that increased by 0.5 mg/dL (versus 1.1% placebo). In the cardiovascular outcomes trial, 7.1% of patients had creatinine values that increased by 0.5 mg/dL (versus 5.5% placebo) and 9.5% of patients in the NEXLETOL group had BUN values that increased ≥ 2× baseline (versus 6.2% placebo).

Decrease in Hemoglobin and Leukocytes

In the hypercholesterolemia trials, approximately 5.1% of patients treated with NEXLETOL (versus 2.3% placebo) had decreases in hemoglobin levels of 2 or more g/dL and below the lower limit of normal on one or more occasion. Anemia was reported in 2.8% of patients treated with NEXLETOL and 1.9% of patients treated with placebo. Approximately 9.0% of NEXLETOL-treated patients with normal baseline leukocyte count had a decrease to less than the lower limit of normal on one or more occasion (versus 6.7% placebo). Leukocyte decrease was generally asymptomatic and did not require medical intervention. In the hypercholesterolemia trials, there was a small imbalance in skin or soft tissue infections, including cellulitis (0.8% versus 0.4%), but there was no imbalance in other infections.

In the cardiovascular outcomes trial, 10.8% of patients (versus 7.4% placebo) had a decrease in hemoglobin of 2 or more g/dL and below the lower limit of normal. Anemia was reported in 4.7% of patients treated with NEXLETOL and 3.9% of patients treated with placebo. There were 9.3% of NEXLETOL-treated patients with a leukocyte count below the lower limit of normal (and normal at baseline) at any point (versus 6.8% placebo).

Increase in Platelet Count

In the hypercholesterolemia trials, approximately 10.1% of patients (versus 4.7% placebo) had increases in platelet counts of 100× 10^9/L or more on one or more occasion. In the cardiovascular outcomes trial, 18.6% of patients in the NEXLETOL-treated group (versus 10.2% placebo) had an increase in platelet count of 100 × 10^9/L or more. Platelet count increase was asymptomatic and did not result in increased risk for thromboembolic events.

Increase in Liver Enzymes

In the hypercholesterolemia trials, increases in hepatic transaminases (AST and/or ALT) were observed with NEXLETOL. In most cases, the elevations were transient and resolved or improved with continued therapy or after discontinuation of therapy. Increases to more than 3× the upper limit of normal (ULN) in AST occurred in 1.4% of patients treated with NEXLETOL versus 0.4% of placebo patients, and increases to more than 5× ULN occurred in 0.4% of NEXLETOL-treated versus 0.2% of placebo-treated patients. Increases in ALT occurred with similar incidence between NEXLETOL- and placebo-treated patients. Elevations in transaminases were generally asymptomatic and not associated with elevations ≥ 2× ULN in bilirubin or with cholestasis.

In the cardiovascular outcomes trial, the incidence of repeated and confirmed ALT and/or AST >3× ULN was 1.6% in the NEXLETOL-treated group (versus 1.0% placebo). A higher percentage of patients in the NEXLETOL-treated group had hepatic enzyme elevations versus placebo (4.5% versus 3.0%, respectively).

Increase in Creatine Kinase

In the hypercholesterolemia trials, approximately 1.0% of patients (versus 0.6% placebo) had elevations of CK levels of 5 or more times the normal value on one or more occasions, and 0.4% of patients (versus 0.2% placebo) had elevations of CK levels of 10 or more times.

6.2 Postmarketing Experience

The following adverse reactions have been identified during post approval use of NEXLETOL. Because these reactions are reported voluntarily from a population of uncertain size, it is not always possible to reliably estimate their frequency or establish a causal relationship to drug exposure.

Immune System Disorders: Hypersensitivity reactions including: angioedema, wheezing, rash, and urticaria.

7 DRUG INTERACTIONS

Table 3 includes a list of drugs with clinically important drug interactions when administered concomitantly with NEXLETOL and instructions for preventing or managing them.

Table 3. Clinically Important Drug Interactions with NEXLETOL
Simvastatin
Clinical Impact: | Concomitant use of NEXLETOL with simvastatin causes an increase in simvastatin concentration and may increase the risk of simvastatin-related myopathy [see Clinical Pharmacology (12.3)].
Intervention: | Avoid concomitant use of NEXLETOL with simvastatin greater than 20 mg.
Pravastatin
Clinical Impact: | Concomitant use of NEXLETOL with pravastatin causes an increase in pravastatin concentration and may increase the risk of pravastatin-related myopathy [see Clinical Pharmacology (12.3)].
Intervention: | Avoid concomitant use of NEXLETOL with pravastatin greater than 40 mg.
Fibrates
Clinical Impact: | Concomitant administration of fibrates with NEXLETOL resulted in increased triglycerides and decreased high-density lipoprotein cholesterol (HDL-C) in some patients in clinical studies and post-marketing reports. Reversibility of both increased triglycerides and decreased HDL-C levels was observed when either NEXLETOL or fibrate therapy was discontinued.
Intervention: | Monitor triglycerides and HDL-C four weeks after initial concomitant use of NEXLETOL and a fibrate and periodically thereafter. If increased triglycerides or decreased HDL-C levels are detected, discontinue NEXLETOL or fibrate therapy based on clinical judgment. Monitor triglycerides and HDL-C levels until levels return to baseline.

8 USE IN SPECIFIC POPULATIONS

8.1 Pregnancy

Risk Summary

Discontinue NEXLETOL when pregnancy is recognized unless the benefits of therapy outweigh the potential risks to the fetus.

There are insufficient data on NEXLETOL use in pregnant women to evaluate for a drug-associated risk of major birth defects, miscarriage, or adverse maternal or fetal outcomes. In animal reproduction studies, bempedoic acid was not teratogenic in rats and rabbits when administered at doses resulting in exposures up to 11 and 12 times, respectively, the human exposures at the maximum clinical dose, based on AUC (see Data). NEXLETOL decreases cholesterol synthesis and possibly the synthesis of other biologically active substances derived from cholesterol; therefore, NEXLETOL may cause fetal harm when administered to pregnant women based on the mechanism of action [see Clinical Pharmacology (12.1)]. In addition, treatment of hypercholesterolemia is not generally necessary during pregnancy. Atherosclerosis is a chronic process and the discontinuation of lipid-lowering drugs during pregnancy should have little impact on the outcome of long-term therapy of primary hypercholesterolemia for most patients.

The estimated background risk of major birth defects and miscarriage for the indicated population is unknown. In the U.S. general population, the estimated background risk of major birth defects and miscarriage in clinically recognized pregnancies is 2-4% and 15-20%, respectively.

Report pregnancies to the Esperion Therapeutics, Inc. Adverse Event reporting line at 1-833-377-7633.

Data

Animal Data

Bempedoic acid was not teratogenic when given orally at doses of 60 and 80 mg/kg/day, resulting in 11 and 12 times the systemic exposure in humans at the maximum recommended human dose (MRHD) of 180 mg to pregnant rats and rabbits, respectively. In an embryofetal development study in rats, bempedoic acid was given orally to pregnant rats at 10, 30, and 60 mg/kg/day during the period of organogenesis from gestation day 6 to 17. There were increases in the incidence of non-adverse fetal skeletal variations (bent long bones and bent scapula and incomplete ossification) at doses ≥ 10 mg/kg/day (less than the clinical exposure) in the absence of maternal toxicity. At maternally toxic doses, bempedoic acid caused decreases in the numbers of viable fetuses, increases in post-implantation loss, and increased total resorptions at 60 mg/kg/day (11 times MRHD) and reduced fetal body weight at ≥ 30 mg/kg/day (4 times the MRHD). No adverse development effects were observed when bempedoic acid was given to pregnant rabbits during the period of organogenesis (gestation day 6 to 18) at doses up to 80 mg/kg/day (12 times MRHD).

In a pre- and post-natal development study in pregnant rats given oral doses of bempedoic acid at 5, 10, 20, 30 and 60 mg/kg/day throughout pregnancy and lactation (gestation day 6 to lactation day 20), there were adverse effects on delivery in the presence of maternal toxicity, including: increases in stillborn pups, reductions in numbers of live pups, pup survival, pup growth and slight delays in learning and memory at ≥ 10 mg/kg/day (at exposures equivalent to the MRHD).

8.2 Lactation

Risk Summary

Bempedoic acid was detected in breast milk of lactating women who received six consecutive daily doses of 180 mg bempedoic acid. The mean daily infant dose of bempedoic acid through breast milk was approximately 0.03 mg/day (95% CI: 0.02; 0.05) with a mean calculated daily infant oral dosage of 0.012 mg/kg/day based on a standard infant milk intake of 150 mL/kg/day. The mean (SD) relative infant dose (RID) was approximately 0.5 (0.2)% of the maternal weight-adjusted dosage (see Data). Concentrations of ESP15228, the active metabolite, in breast milk were below the limit of quantitation (20 ng/mL) in 7 of 8 subjects studied. There is no information regarding the effects of NEXLETOL on the breastfed infant, or the effects on milk production. NEXLETOL decreases cholesterol synthesis and possibly the synthesis of other biologically active substances derived from cholesterol and may cause harm to the breastfed infant. The developmental and health benefits of breastfeeding should be considered along with the mother's clinical need for NEXLETOL and any potential adverse effects on the breastfed infant from NEXLETOL or from the underlying maternal condition [see Clinical Pharmacology (12.1)].

Data

A lactation study in 8 healthy lactating women evaluated the concentrations of bempedoic acid in mature breast milk. NEXLETOL 180 mg oral tablet was given once daily for six consecutive days. The geometric mean estimate of bempedoic acid Cmax in breast milk was 118 ng/mL (range: 79.6 to 251 ng/mL) with a median Tmax of about 3 hours.

8.4 Pediatric Use

The safety and effectiveness of NEXLETOL have not been established in pediatric patients.

8.5 Geriatric Use

Of the 3,009 adult patients in the primary hypercholesterolemia trials of NEXLETOL, 1,753 (58%) were 65 years of age and older, while 478 (16%) were 75 years of age and older.

Of the 13,970 adult patients in the cardiovascular outcomes trial [see Clinical Studies (14.1)], 8,204 (59%) were 65 years of age and older, while 2,107 (15%) were 75 years of age and older.

No overall differences in safety or effectiveness of NEXLETOL have been observed between patients 65 years of age and older and younger adult patients.

8.7 Hepatic Impairment

No dosage adjustment is necessary in patients with mild or moderate hepatic impairment (Child-Pugh A or B) [see Clinical Pharmacology (12.3)]. Patients with severe hepatic impairment (Child-Pugh C) have not been studied.

10 OVERDOSAGE

There is no clinical experience with NEXLETOL overdose. In the event of an overdosage, consider contacting the Poison Help line (1-800-222-1222) or a medical toxicologist for additional overdosage management recommendations.

11 DESCRIPTION

NEXLETOL tablets, for oral use, contain bempedoic acid, an adenosine triphosphate-citrate lyase (ACL) inhibitor. The chemical name for bempedoic acid is 8-hydroxy-2,2,14,14-tetramethyl-pentadecanedioic acid. The molecular formula is C19H36O5, and the molecular weight is 344.5 grams per mole. Bempedoic acid is a white to off-white crystalline powder that is highly soluble in ethanol, isopropanol and pH 8 phosphate buffer, and insoluble in water and aqueous solutions below pH 5.

Structural formula:

Each film-coated tablet of NEXLETOL contains 180 mg of bempedoic acid and the following inactive ingredients: colloidal silicon dioxide, hydroxyl propyl cellulose, lactose monohydrate, magnesium stearate, microcrystalline cellulose, and sodium starch glycolate. The film coating comprises of partially hydrolyzed polyvinyl alcohol, polyethylene glycol, talc, and titanium dioxide.

12 CLINICAL PHARMACOLOGY

12.1 Mechanism of Action

Bempedoic acid is an adenosine triphosphate-citrate lyase (ACL) inhibitor that lowers LDL-C by inhibition of cholesterol synthesis in the liver. ACL is an enzyme upstream of 3-hydroxy-3-methyl-glutaryl-coenzyme A (HMG-CoA) reductase in the cholesterol biosynthesis pathway. Bempedoic acid and its active metabolite, ESP15228, require coenzyme A (CoA) activation by very long-chain acyl-CoA synthetase 1 (ACSVL1) to ETC-1002-CoA and ESP15228-CoA, respectively. ACSVL1 is expressed primarily in the liver. Inhibition of ACL by ETC-1002-CoA results in decreased cholesterol synthesis in the liver and lowers LDL-C in blood via upregulation of low-density lipoprotein receptors.

12.2 Pharmacodynamics

Administration of bempedoic acid alone, or in combination with other lipid modifying agents, decreases LDL-C, non-high density lipoprotein cholesterol (non-HDL-C), apolipoprotein B (apo B), and total cholesterol (TC) in patients with hypercholesterolemia.

Cardiac Electrophysiology

At a dose of 240 mg (1.3 times the approved recommended dose), bempedoic acid does not prolong the QT interval to any clinically relevant extent.

12.3 Pharmacokinetics

Bempedoic acid pharmacokinetic parameters are presented as the mean [± standard deviation (SD)] unless otherwise specified. The steady-state maximum plasma concentration (Cmax) and area under the curve (AUC) following multiple-dose administration of bempedoic acid at 180 mg/day were 20.6 ± 6.1 µg/mL and 289.0 ± 96.4 µg∙h/mL, respectively. Bempedoic acid steady-state pharmacokinetics were generally linear over a range of > 60 mg to 220 mg (approximately 33% to 122% of the recommended dosage of 180 mg daily). There were no time-dependent changes in bempedoic acid pharmacokinetics following repeat administration at the recommended dosage, and bempedoic acid steady-state was achieved after 7 days. The mean accumulation ratio was approximately 2.3-fold.

The steady-state Cmax and AUC of the active metabolite (ESP15228) of bempedoic acid were 2.8 ± 0.9 µg/mL and 51.2 ± 17.2 µg∙h/mL, respectively. ESP15228 likely made a minor contribution to the overall clinical activity of bempedoic acid based on systemic exposure, relative potency, and pharmacokinetic properties.

Absorption

Pharmacokinetic data indicate that bempedoic acid is absorbed with a median time to maximum concentration of 3.5 hours when administered as NEXLETOL 180 mg tablets.

Effect of Food

Concomitant food administration had no effect on the oral bioavailability of bempedoic acid.

Distribution

The bempedoic acid apparent volume of distribution (V/F) was 18 L. Plasma protein binding of bempedoic acid, its glucuronide and its active metabolite, ESP15228, were 99.3%, 98.8% and 99.2%, respectively. Bempedoic acid does not partition into blood cells.

Elimination

The steady-state clearance (CL/F) of bempedoic acid was 11.2 mL/min after once-daily dosing; renal clearance of unchanged bempedoic acid represented less than 2% of total clearance. The mean ± SD half-life for bempedoic acid in humans was 21 ± 11 hours at steady-state.

Metabolism

The primary route of elimination for bempedoic acid is through metabolism of the acyl glucuronide. Bempedoic acid is also reversibly converted to an active metabolite (ESP15228) based on aldo-keto reductase activity observed in vitro from human liver. Mean plasma AUC metabolite/parent drug ratio for ESP15228 following repeat-dose administration was 18% and remained constant over time. Both compounds are converted to inactive glucuronide conjugates in vitro by UGT2B7. Bempedoic acid, ESP15228 and their respective conjugated forms were detected in plasma with bempedoic acid accounting for the majority (46%) of the AUC0-48h and its glucuronide being the next most prevalent (30%). ESP15228 and its glucuronide represented 10% and 11% of the plasma AUC0-48h, respectively.

Excretion

Following single oral administration of 240 mg of bempedoic acid (1.3 times the approved recommended dose), approximately 70% of the total dose (bempedoic acid and its metabolites) was recovered in urine, primarily as the acyl glucuronide conjugate of bempedoic acid, and approximately 30% was recovered in feces. Less than 5% of the administered dose was excreted as unchanged bempedoic acid in feces and urine combined.

Specific Populations

No clinically significant differences in the pharmacokinetics of bempedoic acid were observed based on age, gender, race, weight, renal impairment (mild, moderate, and severe renal impairment or renal failure), or mild (Child-Pugh Class A) and moderate (Child-Pugh Class B) hepatic impairment. The effect of severe (Child-Pugh Class C) hepatic impairment on bempedoic acid pharmacokinetics is unknown.

Drug Interaction Studies

Cytochrome P450 Substrates

In vitro metabolic interaction studies suggest that bempedoic acid, as well as its active metabolite and glucuronide forms are not metabolized by and do not interact with cytochrome P450 enzymes.

Transporter-mediated Drug Interactions

In vitro drug interaction studies suggest bempedoic acid, as well as its active metabolite and glucuronide form, are not substrates of commonly characterized drug transporters with the exception of bempedoic acid glucuronide, which is an OAT3 substrate. Bempedoic acid weakly inhibits OAT3 at high multiples of clinically relevant concentrations, and bempedoic acid and its glucuronide weakly inhibit OATP1B1, and OATP1B3 at clinically relevant concentrations. Bempedoic acid weakly inhibits OAT2 in vitro, which is likely the mechanism responsible for minor elevations in serum creatinine and uric acid [see Adverse Reactions (6.1)].

Probenecid

Administration of bempedoic acid 180 mg with steady-state probenecid resulted in a 1.7- and a 1.2-fold increase in bempedoic acid AUC and Cmax, respectively. AUC and Cmax for bempedoic acid active metabolite (ESP15228) were increased 1.9- and 1.5-fold, respectively. These elevations are not clinically meaningful and do not impact dosing recommendations.

Statins

The pharmacokinetic interactions between bempedoic acid (at systemic exposure relevant to the indicated CVD population) and simvastatin 20 mg, atorvastatin 10 mg, pravastatin 40 mg, and rosuvastatin 10 mg were evaluated in clinical trials.

Simvastatin: Administration of simvastatin 20 mg with 240 mg of bempedoic acid or 40 mg with 180 mg of bempedoic acid in healthy subjects at steady-state resulted in approximately 2-fold (91% for 20 mg and 96% for 40 mg) and 1.5-fold (54% for 20 mg and 52% for 40 mg) increases in simvastatin acid AUC and Cmax, respectively [see Drug Interactions (7)].

Pravastatin: Administration of pravastatin 40 mg with steady-state bempedoic acid 240 mg in healthy subjects resulted in 99% (2-fold) and 104% (2-fold) increases in pravastatin acid AUC and Cmax, respectively [see Drug Interactions (7)].

Atorvastatin and Rosuvastatin: Elevations of 1.7-fold in AUC of atorvastatin, and rosuvastatin and/or their major metabolites were observed, suggesting a weak interaction. These elevations were generally within the individual statin exposures and do not impact dosing recommendations.

Ezetimibe

Increases in AUC and Cmax for ezetimibe were less than 20% when a single dose of ezetimibe was taken with steady-state bempedoic acid. Total ezetimibe (ezetimibe and its glucuronide form) and ezetimibe glucuronide AUC and Cmax increased approximately 1.6- and 1.8-fold, respectively. These elevations are not clinically meaningful and do not impact dosing recommendations.

Warfarin

In vitro studies indicate that bempedoic acid is not an inhibitor or inducer of CYP2C9. Because warfarin is primarily eliminated through CYP2C9, its pharmacokinetics is not expected to be altered by bempedoic acid.

Other

Bempedoic acid had no effect on the pharmacokinetics of metformin or the oral contraceptive Ortho-Novum 1/35.

13 NONCLINICAL TOXICOLOGY

13.1 Carcinogenesis, Mutagenesis, Impairment of Fertility

Bempedoic acid was negative for mutagenicity in an in vitro Ames assay and negative for clastogenicity in the vitro human lymphocyte chromosome aberration assay. Bempedoic acid was negative in both in vivo mouse micronucleus and in vivo rat bone marrow micronucleus/liver comet assay. In a 2-year rat carcinogenicity study, Wistar rats were given oral doses of bempedoic acid at 3, 10 and 30 mg/kg/day. An increased incidence of liver hepatocellular adenomas and hepatocellular adenomas combined with carcinomas, thyroid gland follicular cell adenoma and follicular cell adenomas combined with carcinomas, and pancreatic islet cell adenomas combined with carcinomas were observed in male rats at the dose of 30 mg/kg/day (exposure equivalent to the maximum recommended human dose (MRHD), based on AUC). In a 2-year mice carcinogenicity study, CD-1 mice were given oral doses of bempedoic acid at 25, 75 and 150 mg/kg/day. Bempedoic acid-related increases in the incidence of liver hepatocellular adenomas, hepatocellular carcinomas and hepatocellular adenomas combined with carcinomas in male mice were observed at 75 and 150 mg/kg/day (exposures equivalent to the MRHD). Observations of liver and thyroid tumors are consistent with PPAR alpha agonism in rodents. The human relevance of pancreatic islet cell tumor findings is unknown.

In fertility and early embryofetal development study in rats, bempedoic acid was given orally to male and female rats at 10, 30 and 60 mg/kg/day. Males were dosed for 28 days prior to mating and females were dosed 14 days prior to mating through gestation day 7. No adverse effects on fertility were observed in females in the absence of maternal toxicity. No effects were observed on male fertility outcomes, but decreases in sperm counts were observed at 60 mg/kg/day (9 times the MRHD).

14 CLINICAL STUDIES

14.1 Cardiovascular Outcomes Trial in Adults With CVD or at High Risk for CVD

Trial 1 (NCT02993406) was a randomized, double-blind, placebo-controlled, event-driven trial in 13,970 adult patients with established CVD (70%) or at high risk for a CVD event but without CVD (30%) who were not receiving recommended statin dosages. Patients with established CVD had documented history of coronary artery disease, symptomatic peripheral arterial disease, and/or cerebrovascular atherosclerotic disease. Patients without established CVD were considered at high risk for CVD based on meeting at least one of the following criteria:

(1) Diabetes mellitus (type 1 or type 2) in females over 65 years of age or males over 60 years of age;
(2) A Reynolds Risk score > 30% or a SCORE Risk score > 7.5% over 10 years. Reynolds risk score and SCORE risk score evaluate a 10-year risk of having a cardiovascular (CV) event. The Reynolds risk score is based on the following risk factors: sex, age, smoking status, systolic blood pressure, total cholesterol, HDL cholesterol, high sensitivity C-reactive protein (hsCRP), and familial history of CVD events. LDL-C is an additional risk factor considered in SCORE risk score; or
(3) A coronary artery calcium score >400 Agatston units at any time in the past.

Patients were randomized 1:1 to receive either oral NEXLETOL 180 mg per day (n = 6,992) or placebo (n = 6,978), alone or as an add on to other background lipid-lowering therapies. Background therapy could include less than low-intensity statin dosages. Overall, 95.3% of adult patients were followed until the end of the trial or death. The median follow-up duration was 3.4 years.

Baseline Demographics and Disease Characteristics

At baseline, the mean age was 66 years (range 21 to 92 years), 59% were 65 years of age and older, 15% were 75 years of age and older, 48% were female, 91% were White, 2% were Black or African American, 4% were American Indian or Alaska Native, 2% were Asian, and 1% were other races; 17% identified as Hispanic or Latino ethnicity.

Selected additional baseline characteristics included hypertension (85%), diabetes mellitus (46%), current tobacco user (22%), eGFR < 60 mL/min per 1.73 m^2 (21%), and a mean body mass index of 30 kg/m^2. The mean baseline LDL-C was 139 mg/dL. At baseline, 38% of patients were taking at least one lipid-modifying therapy, including less than low-intensity statin dosages (23%), ezetimibe (12%), or fibrates (5%). Most patients were taking at least one other CV medication including acetylsalicylic acid (57%), selective beta blockers (52%), angiotensin converting enzyme inhibitors (40%), or angiotensin receptor blockers (32%).

Efficacy Results

The risk for the primary composite endpoint (MACE-4: time to first occurrence of CV death, nonfatal myocardial infarction, nonfatal stroke, or coronary revascularization; p= 0.0037) and the key secondary composite endpoint (MACE-3: time to first occurrence of CV death, nonfatal myocardial infarction, or nonfatal stroke; p= 0.0058) was significantly reduced in NEXLETOL-treated patients compared to placebo-treated patients (see Table 4). The difference between the NEXLETOL and placebo groups in mean percent change in LDL-C from baseline to Month 6 was -20% (95% CI: -21%, -19%).

Table 4: Major Cardiovascular Events in Adults with Established CVD or at High Risk for CVD (Trial 1)
 | NEXLETOL N=6,992 | Placebo N=6,978 | NEXLETOL vs. Placebo
Endpoint | n (%) | n (%) | Hazard Ratio (95% CI)
Primary Composite Endpoint
Cardiovascular death, non-fatal myocardial infarction, non-fatal stroke, coronary revascularization (MACE-4) | 819 (11.7) | 927 (13.3) | 0.87 (0.79, 0.96)
Key Secondary Endpoint
Cardiovascular death, non-fatal myocardial infarction, non-fatal stroke (MACE-3) | 575 (8.2) | 663 (9.5) | 0.85 (0.76, 0.96)
Components of Primary Composite Endpoint
Non-fatal myocardial infarction | 236 (3.4) | 317 (4.5) | 0.73 (0.62, 0.87)
Coronary revascularization | 435 (6.2) | 529 (7.6) | 0.81 (0.72, 0.92)
Non-fatal stroke | 119 (1.7) | 144 (2.1) | 0.82 (0.64, 1.05)
Cardiovascular death | 269 (3.8) | 257 (3.7) | 1.04 (0.88, 1.24)
CI = confidence interval; MACE = major adverse cardiac event.
aHazard ratio and corresponding 95% CI were based on a Cox proportional hazard model fitting treatment as explanatory variable.
This table also presents the time to first occurrence for each of the components of MACE-4; patients may have been included in more than one category

The Kaplan-Meier estimates of the cumulative incidence of the MACE-4 and MACE-3 endpoints are shown in Figure 1 and 2 below.

Figure 1: Cumulative Incidence of Primary Composite Endpoint (MACE-4) Over 4.5 Years in Adults with Established CVD or at High Risk for CVD (Trial 1)

MACE = major adverse cardiac event
MACE-4 was defined as the time to first occurrence of the composite endpoint of CV death, nonfatal MI, nonfatal stroke, or coronary revascularization.

Figure 2: Cumulative Incidence of Composite Endpoint (MACE-3) Over 4.5 Years in Adults with Established CVD or at High Risk for CVD (Trial 1)

MACE = major adverse cardiac event
MACE-3 was defined as time to first occurrence of the composite endpoint of CV death, nonfatal MI, or nonfatal stroke.

14.2 Primary Hypercholesterolemia Trials in Adults

The efficacy of NEXLETOL as an adjunct to diet and statin therapy, to reduce elevated LDL-C in adults with primary hypercholesterolemia (including HeFH) was investigated in two multi-center, randomized, double-blind, placebo-controlled trials that enrolled 3,009 adult patients with HeFH or established CVD who were on maximally tolerated statin therapy (Trials 2 and 3). Demographics and baseline disease characteristics were balanced between the treatment arms in these trials. In both trials, the maximum LDL-C lowering effects occurred at Week 4. These results were consistent across all subgroups studied in any of the trials, including age, sex, race, ethnicity, region, history of diabetes, baseline LDL-C, body mass index (BMI), HeFH status, and background therapies.

Trial 2 (NCT02666664)

Trial 2 was a multi-center, randomized, double-blind, placebo-controlled, primary hypercholesterolemia (52-week) trial in adult patients with HeFH and/or CVD. Efficacy of NEXLETOL was evaluated at Week 12. The trial included 2,230 patients randomized 2:1 to receive either oral NEXLETOL (n = 1,488) or placebo (n = 742) as add-on to a maximally tolerated lipid-lowering therapy. Maximally tolerated lipid-lowering therapy was defined as a maximally tolerated statin dose alone or in combination with other lipid-lowering therapies. Patients were stratified by presence of HeFH and by baseline statin intensity. Patients on simvastatin 40 mg per day or higher and patients taking PCSK9 inhibitors were excluded from the trial.

Baseline Demographics and Disease Characteristics: Overall, the mean age at baseline was 66 years (range: 24 to 88 years), 61% were 65 years of age and older, 27% were female, 96% were White, 3% were Black or African American , and 1% were Asian; 2% identified as Hispanic or Latino ethnicity. Ninety-five percent (95%) of patients had established CVD, and 5% of patients had HeFH. Twenty-nine percent (29%) of patients had diabetes at baseline. The mean baseline LDL-C was 103.2 mg/dL. At the time of randomization, all patients were receiving statin therapy and 50% were receiving high-intensity statin therapy.

Efficacy Results: The primary efficacy outcome measure of the trial was the percent change from baseline to Week 12 in LDL-C. The difference between the NEXLETOL and placebo groups in mean percent change in LDL-C from baseline to Week 12 was -18% (95% CI: -20%, -16%; p < 0.001). High-density lipoprotein (HDL) and triglycerides (TG) were examined as exploratory endpoints and were not included in the statistical hierarchy. The difference between the NEXLETOL and placebo groups in mean percent change from baseline to Week 12 was -6% for HDL and median percent change from baseline to Week 12 was +3% for TG. For additional results see Table 4 and Figure 3.

Table 4: Lipid Parameters in Adult Patients with HeFH and/or CVD on Maximally Tolerated Statin Therapy (Mean % Change from Baseline to Week 12 in Trial 2)
 | LDL-C [4.3% of subjects on NEXLETOL and 2.3% of patients on placebo had missing LDL-C data at primary endpoint (Week 12). By the end of the trial (Week 52), 8.3% of patients on NEXLETOL and 7.7% of patients on placebo had missing LDL-C measurements.] , [Percent change from baseline was analyzed using analysis of covariance (ANCOVA), with treatment and randomization strata (HeFH versus CVD, and high intensity statin versus other statin) as factors and baseline lipid parameter as a covariate. Missing data for LDL-C, non-HDL-C, TC and apo B were imputed through multiple imputation using a pattern mixture model (PMM) account for treatment adherence.] | Non-HDL-C | apo B | TC
NEXLETOL (180 mg/day; n = 1488 [Number of randomized subjects at baseline]) | -17 | -12 | -9 | -10
Placebo (n = 742) | 2 | 2 | 3 | 1
Mean Difference from Placebo (95% CI) | -18 (-20, -16) | -13 (-15, -12) | -12 (-14, -10) | -11 (-13, -10)
apo B = apolipoprotein B; CI = confidence interval; HDL-C = high-density lipoprotein cholesterol; LDL-C = low-density lipoprotein cholesterol; TC = total cholesterol.
Background statin: atorvastatin, simvastatin, pravastatin, and/or other lipid-lowering therapies

Trial 3 (NCT02991118)

Trial 3 was a multi-center, randomized, double-blind, placebo-controlled, primary hypercholesterolemia (52-week) trial in patients with HeFH and/or CVD. Efficacy of NEXLETOL was evaluated at Week 12. The trial included 779 patients randomized 2:1 to receive either oral NEXLETOL (n = 522) or placebo (n = 257) as add-on to a maximally tolerated lipid-lowering therapy. Maximally tolerated lipid-lowering therapy was defined as a maximally tolerated statin dose alone or in combination with other lipid-lowering therapies. Patients were stratified by presence of HeFH and baseline statin intensity. Patients on simvastatin 40 mg/day or higher were excluded from the trial.

Baseline Demographics and Disease Characteristics: Overall, the mean age at baseline was 64 years (range: 28 to 91 years), 51% were 65 years of age and older, 36% were female, 94% were White, 5% were Black or African American, and 1% were Asian; 8% identified as Hispanic or Latino ethnicity. Ninety-five percent (95%) of patients had established CVD, and 5% of patients had HeFH. Thirty percent (30%) of patients had diabetes at baseline. The mean baseline LDL-C was 120.4 mg/dL. At the time of randomization, 90% of patients were receiving statin therapy, 53% were receiving high-intensity statin therapy, and 0.3% were receiving PCSK9 inhibitors.

Efficacy Results: The primary efficacy outcome measure of the trial was the percent change from baseline to Week 12 in LDL-C. The difference between the NEXLETOL and placebo groups in mean percent change in LDL-C from baseline to Week 12 was -17% (95% CI: -21%, -14%; p < 0.001). HDL and TG were exploratory endpoints and not included in the statistical hierarchy. The difference between the NEXLETOL and placebo groups in mean percent change from baseline to Week 12 was -6% for HDL and the median percent change from baseline was -2% for TG. For additional results see Table 5 and Figure 3.

Table 5. Lipid Parameters in Adult Patients with HeFH and/or CVD on Maximally Tolerated Statin Therapy (Mean % Change from Baseline to Week 12 in Trial 3)
 | LDL-C [4.6% of patients on NEXLETOL and 1.6% of patients on placebo had missing LDL-C data at primary endpoint (Week 12). By the end of the trial (Week 52), 10.5% of patients on NEXLETOL and 7.8% of patients on placebo had missing LDL-C measurements.] , [Percent change from baseline was analyzed using analysis of covariance (ANCOVA), with treatment and randomization strata (HeFH versus CVD, and high intensity statin versus other statin) as factors and baseline lipid parameter as a covariate. Missing data for LDL-C, non-HDL-C, TC and apo B were imputed through multiple imputation using a pattern mixture model (PMM) account for treatment adherence.] | Non-HDL-C | apo B | TC
NEXLETOL (180 mg/day; n = 522 [Number of randomized patients at baseline]) | -15 | -11 | -9 | -10
Placebo (n = 257) | 2 | 2 | 4 | 1
Difference from Placebo (95% CI) | -17 (-21, -14) | -13 (-16, -10) | -13 (-16, -10) | -11 (-14, -9)
apo B = apolipoprotein B; CI = confidence interval; HDL-C = high-density lipoprotein cholesterol; LDL-C = low-density lipoprotein cholesterol; TC = total cholesterol.
Background statin: atorvastatin, simvastatin, rosuvastatin, pravastatin, fluvastatin, pitavastatin, and lovastatin ± other lipid-lowering therapies

Figure 3: Mean Percent Change from Baseline in LDL-C Over 52 Weeks in Adult Patients with HeFH and/or CVD on Maximally Tolerated Statin Treated with NEXLETOL or Placebo (Trial 2 and Trial 3)

LDL-C derived is calculated from the Friedewald equation: LDL-C = TC - HDL-C - TG/5 in mg/dL.
The error bars represent standard error.

16 HOW SUPPLIED/STORAGE AND HANDLING

How Supplied

NEXLETOL tablets are supplied as follows:

Tablet Strength | Description | Package Configuration | NDC No.
180 mg | White to off white and oval, debossed with "180" on one side and "ESP" on the other side | Bottle of 30 tablets with child-resistant cap | 72426-118-03

Storage and Handling

Store at 68°F to 77°F (20°C to 25°C); excursions permitted to 59°F to 86°F (15°C to 30°C) [see USP Controlled Room Temperature]. Store and dispense in the original package.

17 PATIENT COUNSELING INFORMATION

Advise patients to read the FDA-approved patient labeling (Patient Information).

Risk of Hyperuricemia

Advise patients of the risk of elevated serum uric acid levels, including development of gout. Inform patients that serum uric acid levels may be monitored during treatment with NEXLETOL. Patients with signs or symptoms of hyperuricemia should contact their healthcare provider if symptoms occur [See Warnings and Precautions (5.1)]

Risk of Tendon Rupture

Inform patients of the risk of tendon rupture. Advise patients to rest at the first sign of tendinitis or tendon rupture and to immediately contact their healthcare provider if tendinitis or tendon rupture symptoms occur [see Warnings and Precautions (5.2)].

Risk of Myopathy with Concomitant Use of Simvastatin or Pravastatin

Advise patients to notify their healthcare provider(s) if they are taking, or plan to take simvastatin or pravastatin. The risk of myopathy occurring with the use of simvastatin or pravastatin may be increased when taken with NEXLETOL [see Drug Interactions (7)].

Pregnancy

Advise pregnant women of the potential risk to a fetus based on NEXLETOL's mechanism of action. Advise females to inform their healthcare provider of a known or suspected pregnancy. Advise patients that there is a pregnancy safety study that monitors pregnancy outcomes in patients exposed to NEXLETOL during pregnancy. Encourage these patients to report their pregnancy to Esperion at 1-833-377-7633 [see Use in Specific Populations (8.1)].

Manufactured for:
Esperion Therapeutics, Inc.
3891 Ranchero Drive, Suite 150
Ann Arbor, MI 48108

NEXLETOL® (bempedoic acid) tablets
© 2026 Esperion Therapeutics, Inc.

PATIENT INFORMATION
NEXLETOL® (NEX-le-tol)
(bempedoic acid)
tablets, for oral use

What is NEXLETOL?
NEXLETOL is a prescription medicine used:

- to lower the risk of major adverse cardiovascular (CV) events such as death from cardiovascular disease, heart attack, stroke, or heart procedures like stent placement or bypass surgery in adults at increased risk for these events who are unable to take recommended statin treatment (a cholesterol lowering medicine) or are not taking a statin.
- along with diet and exercise and other cholesterol-lowering medicines, or alone when use with other cholesterol-lowering medicines is not possible, to reduce low-density lipoprotein (LDL, or bad cholesterol) in adults with high blood cholesterol levels called hypercholesterolemia, including a type of high blood cholesterol called heterozygous familial hypercholesterolemia (HeFH).

It is not known if NEXLETOL is safe and effective in children.

Do not take NEXLETOL if you are allergic to bempedoic acid or any of the ingredients in NEXLETOL. See the end of this leaflet for a complete list of ingredients in NEXLETOL. Stop taking NEXLETOL and call your healthcare provider or go to the nearest hospital emergency room right away if you have any signs or symptoms of an allergic reaction including:

- swelling of your face, lips, mouth or tongue
- wheezing
- severe itching
- fast heart beat or pounding in your chest

- trouble breathing
- skin rashes, redness, or swelling
- dizziness or fainting

Before you start taking NEXLETOL, tell your healthcare provider about all your medical conditions, including if you:

- have or had gout.
- have or had tendon problems.
- are pregnant or think you may be pregnant. Tell your healthcare provider right away if you become pregnant while taking NEXLETOL. You and your healthcare provider will decide if you should take NEXLETOL while you are pregnant. If you are pregnant during NEXLETOL treatment, you are encouraged to call Esperion at 1-833-377-7633 to share information about the health of you and your baby.
- are breastfeeding or plan to breastfeed. NEXLETOL may pass into your breastmilk. You and your healthcare provider should decide if you will take NEXLETOL or breastfeed.
- have severe liver problems.

NEXLETOL may affect the way other medicines work, and other medicines may affect how NEXLETOL works. Tell your healthcare provider about all the medicines you take, including prescription and over-the-counter medicines, vitamins, and herbal supplements.
Especially tell your healthcare provider if you take or plan to take:

- simvastatin or pravastatin (other cholesterol-lowering medicines). Taking simvastatin or pravastatin with NEXLETOL may increase your risk of developing muscle pain or weakness (myopathy).
- fibrates (triglyceride-lowering medicines). Taking a fibrate medicine with NEXLETOL may lead to increases in triglycerides (fat in the blood) and decreases in high-density lipoprotein (HDL, good cholesterol).

Know the medicines you take. Keep a list of them to show your healthcare provider and pharmacist when you get a new medicine.

How should I take NEXLETOL?

- Take NEXLETOL exactly as your healthcare provider tells you to take it. Check with your healthcare provider or pharmacist if you are not sure.
- Take 1 NEXLETOL tablet by mouth each day.
- You may take NEXLETOL with or without food.
- Your healthcare provider may do blood tests to check your LDL-C levels between 8 to 12 weeks after starting treatment with NEXLETOL.
- In case of overdose, get medical help or contact a live Poison Center expert right away at 1-800-222-1222. Advice is also available online at poisonhelp.org.

What are possible side effects of NEXLETOL?
NEXLETOL may cause serious side effects, including:

- increased levels of uric acid in your blood (hyperuricemia). This can happen within 4 weeks of you starting NEXLETOL and continue throughout your treatment. Your healthcare provider may monitor your blood uric acid levels while you are taking NEXLETOL. High levels of blood uric acid may lead to gout. Call your healthcare provider if you have the following symptoms of hyperuricemia and gout:

- severe foot pain especially in the toe joint
- warm joints
- swelling

- tender joints
- joint redness

- tendon rupture or injury. Tendon problems can happen in people who take NEXLETOL. Tendons are tough cords of tissue that connect muscles to bones. Symptoms of tendon problems may include pain, swelling, tears, and inflammation of tendons, most commonly with the rotator cuff (the shoulder), the biceps tendon (upper arm), and Achilles tendon at the back of the ankle. This can also happen with other tendons. Tendon ruptures can happen within weeks or months of starting NEXLETOL.
  - The risk of getting tendon problems while you take NEXLETOL is higher if you:

- are over 60 years of age
- are taking antibiotics (fluoroquinolones)
- have had tendon problems

- are taking steroids (corticosteroids)
- have renal failure

- Stop taking NEXLETOL immediately and get medical help right away if you get any of the following signs or symptoms of a tendon rupture:
  - hear or feel a snap or pop in a tendon area
  - bruising right after an injury in a tendon area
  - unable to move the affected area or put weight on the affected area
  Avoid exercise and using the affected area.

The most common side effects of NEXLETOL in people with primary hypercholesterolemia include:

- symptoms of the common cold, flu, or flu-like symptoms
- muscle spasms
- back pain
- stomach pain

- bronchitis
- pain in shoulder, legs, or arms
- anemia
- increased liver enzymes

The most common side effects of NEXLETOL in people with heart problems include:

- kidney problems
- anemia
- increased liver enzymes

- muscle spasms
- gallstones

Tell your healthcare provider if you have any side effect that bothers you or that does not go away. These are not all the possible side effects of NEXLETOL.
For more information, ask your healthcare provider or pharmacist. Call your doctor for medical advice about side effects. You may report side effects to FDA at 1-800-FDA-1088.

How should I store NEXLETOL?

- Store NEXLETOL in the original package at room temperature between 68ºF to 77ºF (20ºC to 25ºC).

Keep NEXLETOL and all medicines out of the reach of children.

General information about the safe and effective use of NEXLETOL.
Medicines are sometimes prescribed for purposes other than those listed in a Patient Information leaflet. Do not use NEXLETOL for a condition for which it was not prescribed. Do not give NEXLETOL to other people, even if they have the same symptoms that you have. It may harm them.
You can ask your pharmacist or healthcare provider for information about NEXLETOL that is written for healthcare professionals.

What are the ingredients in NEXLETOL?

- active ingredient: bempedoic acid
- inactive ingredients: colloidal silicon dioxide, hydroxyl propyl cellulose, lactose monohydrate, magnesium stearate, microcrystalline cellulose, and sodium starch glycolate
- tablet coating: partially hydrolyzed polyvinyl alcohol, polyethylene glycol, talc, and titanium dioxide

Manufactured for:
Esperion Therapeutics, Inc.
3891 Ranchero Drive, Suite 150
Ann Arbor, MI 48108
© 2026 Esperion Therapeutics, Inc.

This Patient Information has been approved by the U.S. Food and Drug Administration

Revised: 01/2026

PRINCIPAL DISPLAY PANEL - 180 mg Tablet Bottle Label

NDC 72426-118-03
Rx only

NEXLETOL®
(bempedoic acid) tablets

Contains
30 Tablets

180 mg